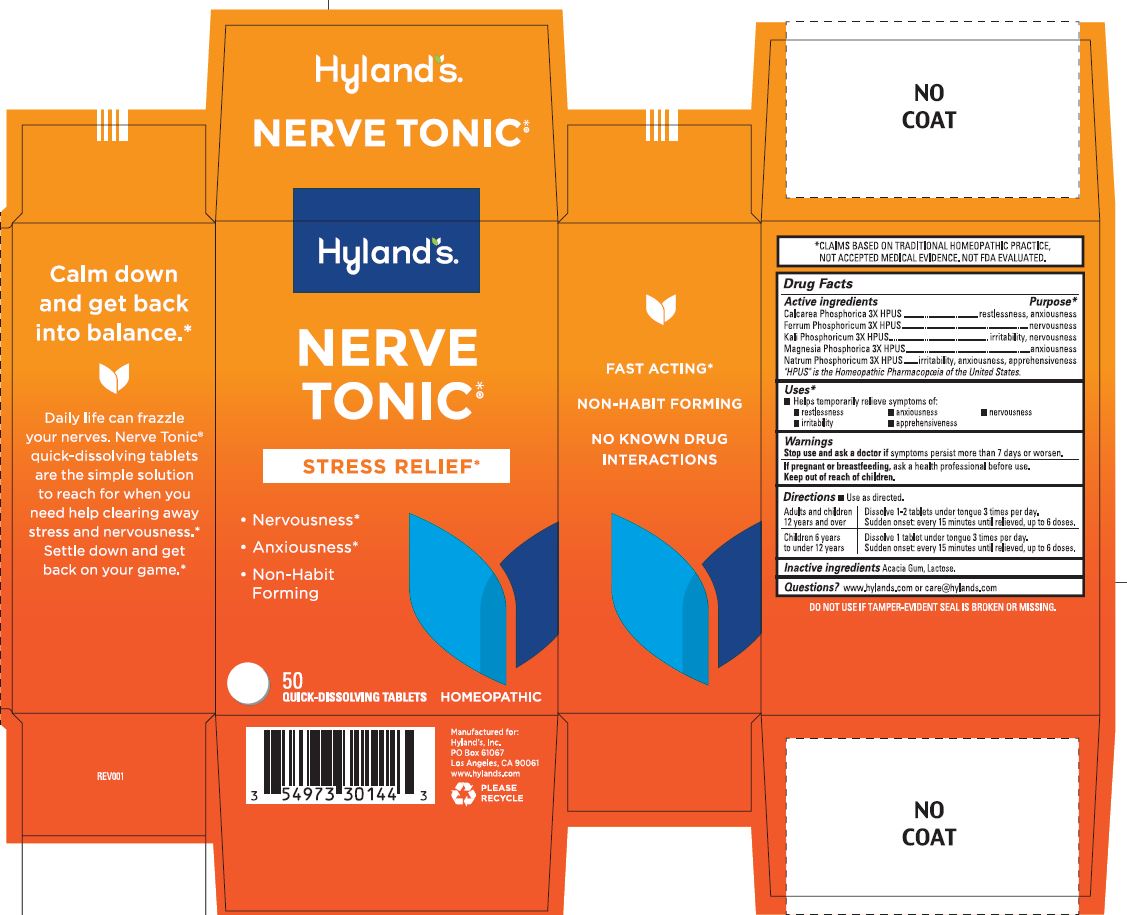 DRUG LABEL: NERVE TONIC
NDC: 54973-3014 | Form: TABLET
Manufacturer: Hyland's Inc.
Category: homeopathic | Type: HUMAN OTC DRUG LABEL
Date: 20250410

ACTIVE INGREDIENTS: CALCIUM PHOSPHATE, UNSPECIFIED FORM 3 [hp_X]/1 1; IRON 3 [hp_X]/1 1; POTASSIUM PHOSPHATE, UNSPECIFIED FORM 3 [hp_X]/1 1; MAGNESIUM PHOSPHATE, DIBASIC TRIHYDRATE 3 [hp_X]/1 1; SODIUM PHOSPHATE 3 [hp_X]/1 1
INACTIVE INGREDIENTS: LACTOSE, UNSPECIFIED FORM

Nerve Tonic

PURPOSE

stress relief, calms nervousness

Drug Facts

Active ingredients

Active ingredients | Purpose
Calcarea Phosphorica 3X HPUS | restlessness, anxiousness
Ferrum Phosphoricum 3X HPUS | nervousness
Kali Phosphoricum 3X HPUS | irritability,nervousness
Magnesia Phosphorica 3X HPUS | anxiousness
Natrum Phosphoricum 3X HPUS | irritability,apprehensiveness

“HPUS” indicates that the active ingredients are in the official Homeopathic Pharmacopœia of the United States.

Uses

■ Temporarily relieves the symptoms of: ■ restlessness ■ anxiousness ■ nervousness ■ irritability ■ apprehensiveness

Warnings

Stop use and ask a doctor if

Symptoms persist more than 7 days or worsen.

If pregnant or breastfeeding

Ask a health professional before use.

Directions

■ Use as directed.

Adults and children 12 years and over | Dissolve 1-2 tablets under tongue 3 times per day. Sudden onset: every 15 minutes until relieved, up to 6 doses.
Children 6 years to under 12 years | Dissolve 1 tablet under tongue 3 times per day. Sudden onset: every 15 minutes until relieved, up to 6 doses.

Inactive ingredients

Acacia Gum, Lactose.

Questions?

www.hylands.com or (800) 624-9659

Indications and Usage

Uses

■ Temporarily relieves the symptoms of: ■ restlessness ■ anxiousness ■ nervousness ■ irritability ■ apprehensiveness

Dosage and Administration

Directions

Adults and children 12 years and over: Dissolve 1-2 tablets under tongue, up to 3 times per day. Sudden onset: every 15 minutes until relieved, up to 6 doses.

Children 6 years to under 12 years: Dissolve 1 tablet under tongue, up to 3 times per day. Sudden onset: every 15 minutes until relieved, up to 6 doses.

Packaging Label - 50 Tablet Bottle Carton

Hyland's

NERVE

TONIC®

STRESS RELIEF*

Nervousness

Anxiousness

Non-Habit

Forming

50

QUICK-DISSOLVING TABLETS

HOMEOPATHIC